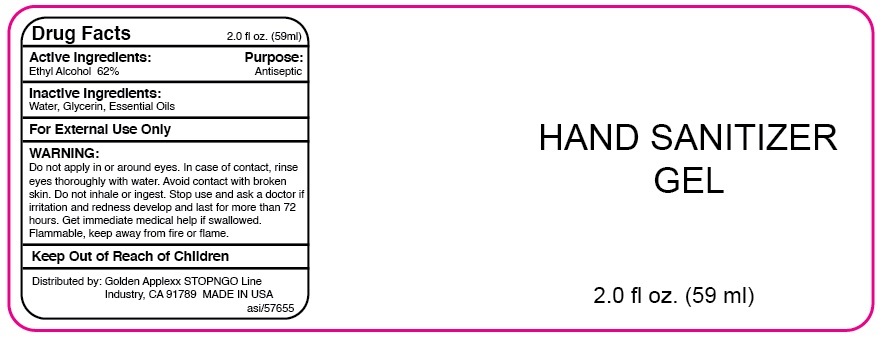 DRUG LABEL: HAND SANITIZER
NDC: 73742-101 | Form: GEL
Manufacturer: Golden Applexx Co., Inc.
Category: otc | Type: HUMAN OTC DRUG LABEL
Date: 20220119

ACTIVE INGREDIENTS: ALCOHOL 0.62 mL/1 mL
INACTIVE INGREDIENTS: WATER; GLYCERIN

HAND SANITIZER

Active Ingredients:

Ethyl Alcohol 62%

Purpose:

Antiseptic

Uses:

• hand sanitizer to decrease bacteria on the skin

• recommended for repeated use

• for use when soap and water are not available

WARNING:

For External Use Only

Do not apply in or around eyes. In case of contact, rinse eyes thoroughly with water. Avoid contact with broken skin. Do not inhale or ingest. Stop use and ask a doctor if irritation and redness develop and last for more than 72 hours. Get immediate medical help if swallowed.
Flammable, keep away from fire or flame.

Directions:

• wet hands thoroughly with product and allow to dry without wiping

• supervise children under 6 years of age when using this product to avoid swallowing

Inactive Ingredients:

Water, Glycerin, Essential Oils

Distributed by: Golden Applexx STOPNGO Line Industry, CA 91789

MADE IN USA